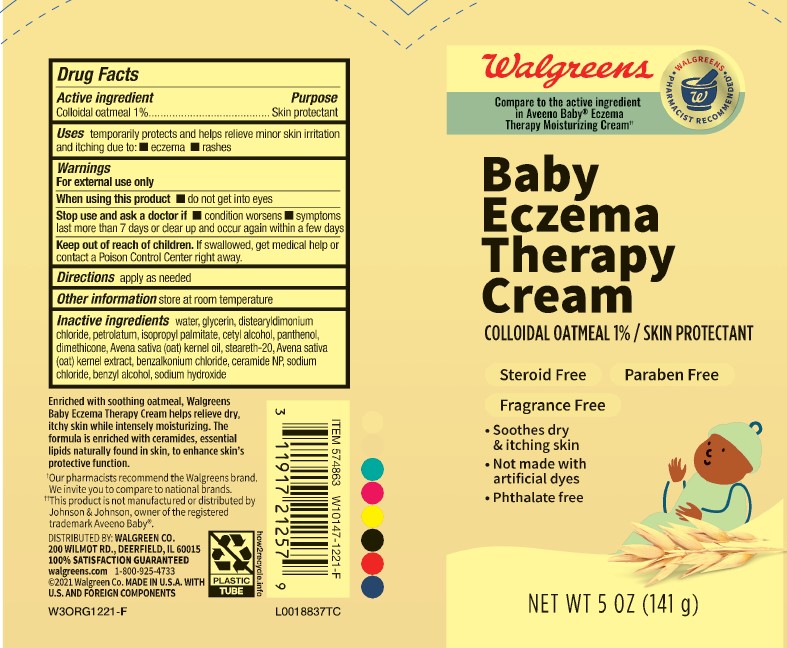 DRUG LABEL: Baby Eczema Therapy
NDC: 0363-0986 | Form: CREAM
Manufacturer: Walgreen Co.
Category: otc | Type: HUMAN OTC DRUG LABEL
Date: 20260212

ACTIVE INGREDIENTS: OATMEAL 10 mg/1 g
INACTIVE INGREDIENTS: GLYCERIN; DISTEARYLDIMONIUM CHLORIDE; PETROLATUM; ISOPROPYL PALMITATE; WATER; CETYL ALCOHOL; PANTHENOL; DIMETHICONE, UNSPECIFIED; OAT KERNEL OIL; STEARETH-20; OAT; BENZALKONIUM CHLORIDE; CERAMIDE NP; SODIUM CHLORIDE; BENZYL ALCOHOL; SODIUM HYDROXIDE

Walgreens 601.000/601AA-AB
Baby Eczema Therapy Cream

Active ingredients

Colloidal oatmeal 1%

Purpose

Skin protectant

Uses

temporarily protects and helps relieve minor skin irritation and itching due to:

- eczema
- rashes

Warnings

For external use only

When using this product

- do not get into eyes

Stop use and ask a doctor if

- condition worsens
- symptoms last more than 7 days or clear up and occur again within a few days

Keep out of reach of children

If swallowed, get medical help or contact a Poison Control Center right away.

Directions

apply as needed

Other information

store at room temperature

Inactive ingredients

water, glycerin, distearyldimonium chloride, petrolatum, isopropyl palmitate, cetyl alcohol, panthenol, dimethicone, Avena sativa (oat) kernel oil, steareth-20, Avena sativa (oat) kernel extract, benzalkonium chloride, ceramide NP, sodium chloride, benzyl alcohol, sodium hydroxide

disclaimer

Enriched with soothing oatmeal, Walgreens Baby Eczema therapy Cream helps relieve dry, itchy skin while intensely moisturizing. The formula is enriched with ceramides, essential lipids naturally found in skin, to enhance skin's protective function.

†Our pharmacists recomment the Walgreens brand. We invite you to compare to national brands.

††This product is not manufactured or distributed by Johnson & Johnson, owner of the registered trademark Aveeno Baby®.

Adverse reactions

DISTRIBUTED BY: WALGREEN CO.

200 WILMOT RD., DEERFIELD, IL 60015

100% SATISFACTION GUARANTEED

walgreens.com 1-800-925-4733

©2021 Walgreen Co.

MADE IN U.S.A. WITH U.S. AND FOREIGN COMPONENTS

PLASTIC TUBE

how2recycle.info

principal display palnel

Walgreens

WALGREENS PHARMACIST RECOMMENDED†

Compare to the active ingredient in Aveeno Baby®Eczema Therapy Moisturizing Cream††

Baby Eczema Therapy Cream

COLLOIDAL OATMEAL 1% / SKIN PROTECTANT

STEROID FREE

PARABEN FREE

FRAGRANCE FREE

- Soothes dry & itching skin
- Not made with artifical dyes
- Phthalate free

NET WT 5 OZ (141 g)